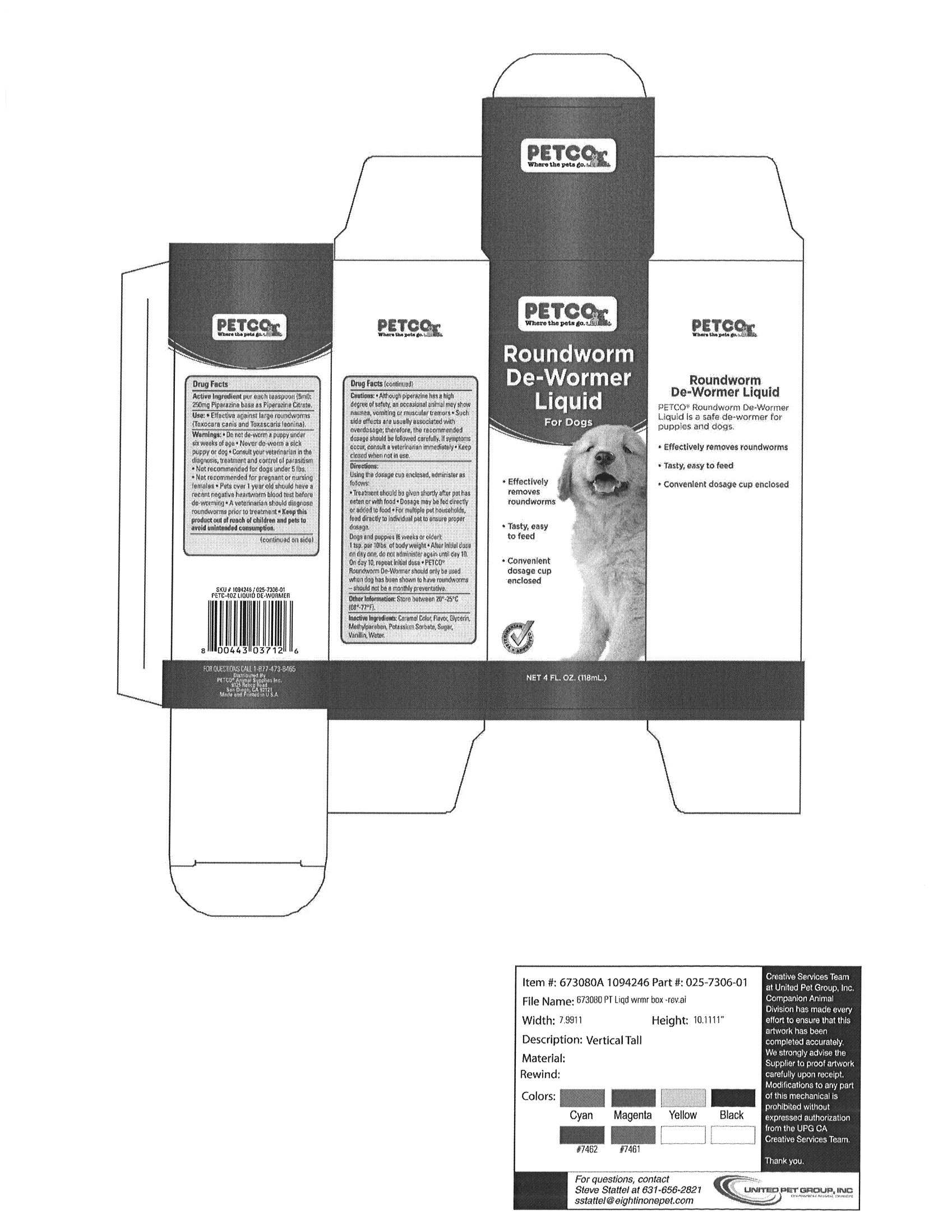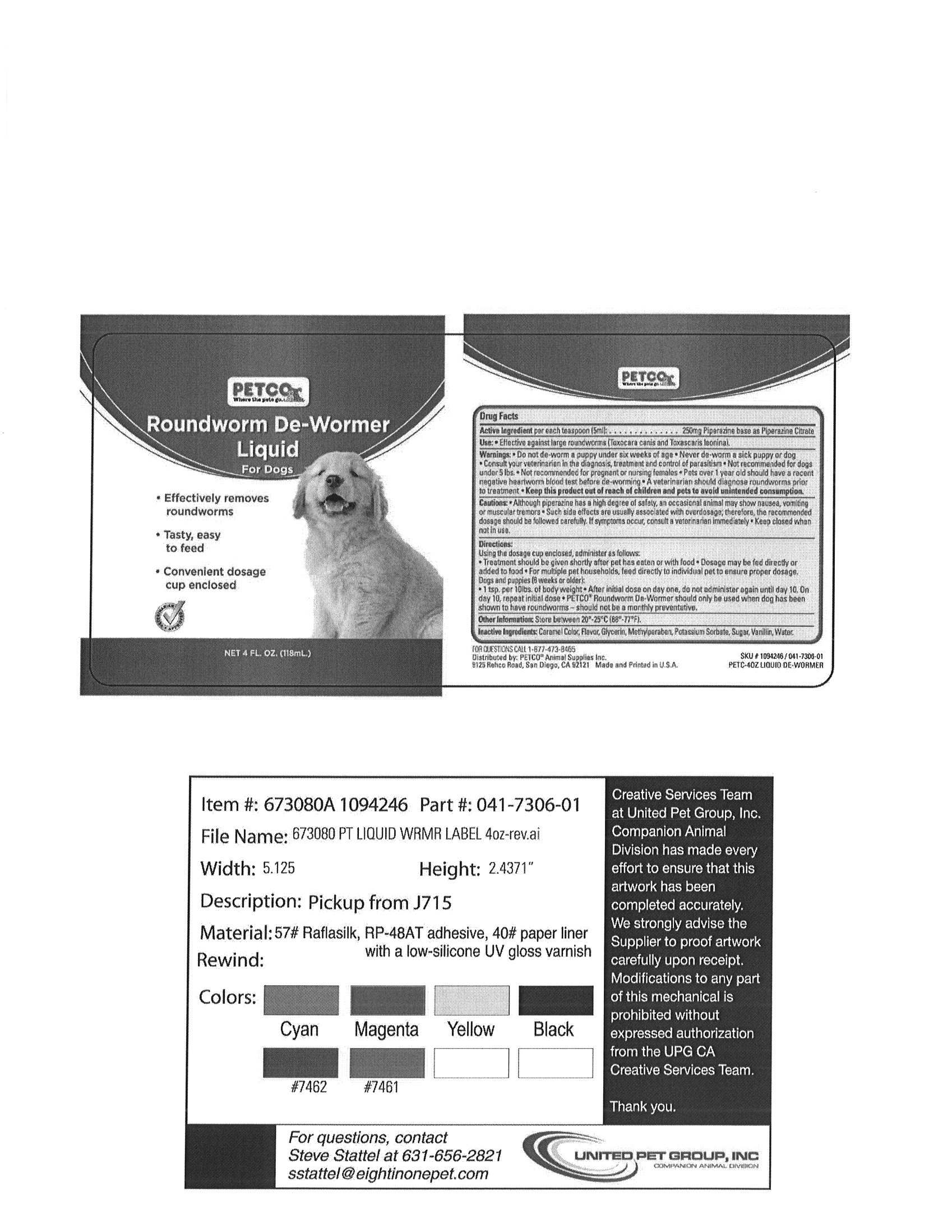 DRUG LABEL: PETCO
NDC: 27102-803 | Form: LIQUID
Manufacturer: Petco
Category: animal | Type: OTC ANIMAL DRUG LABEL
Date: 20100302

ACTIVE INGREDIENTS: PIPERAZINE CITRATE 50 mg/1 mL
INACTIVE INGREDIENTS: GLYCERIN; VANILLIN; METHYLPARABEN; POTASSIUM SORBATE; RAW SUGAR; WATER

Drug Facts

Active Ingredient

per each teaspoon (5ml).................. 250mg Piperazine base as Piperazine Citrate

Use

Effective against large roundworms (Toxocara canis and Toxascaris leonina)

Warnings

Do not de-worm a puppy under six weeks of age. Never de-worm a sick puppy or dog. Consult your veterinarian in the diagnosis, treatment and control of parasitism. Not recommended for dogs under 5lbs. Not recommended for pregnant or nursing females. Pets over 1 year old should have a recent negative heartworm blood test before de-worming. A veterinarian should diagnose roundworms prior to treatment. Keep this product out of reach of children and pets to avois unintended consumption.

Cautions

Although Piperazine has a high degree of safety, an occasional animal may show nausea, vomiting or muscular tremors. Such side effects are usually associated with over dosage, therefore, the recommended dosage should be followed carefully. If symptoms occur, consult a veterinarian immediately. Keep closed when not in use. Keep this product out of reach of children and pets to avoid unintended consumption.

Directions

Using the dosage cup enclosed, administer as follows::
Treatment should be given shortly after pet has eaten or with food. Dosage may be fed directly or added with food. For multiple pet households, feed directly to individual pet to ensure proper dosage.
Dogs and Puppies (6 weeks and older): 1 tsp. per 10lbs. of body weight.
After initial dose on day one, do not administer again until day 10. On day 10, repeat initial dose. PETCO* Roundworm De-wormer should only be used when dog has been shown to have roundworms - should not be used as a monthly preventative.

Other Information

Store between 20C-25C (68F-77F)

Inactive Ingredients

Caramel Color, Flavor, Glycerin, Methylparaben, Potassium Sorbate, Sugar, Vanillin, Water.

FOR QUESTIONS CALL 1-877-473-8465

PACKAGE LABEL

PETCO
Roundworm De-Wormer
Liquid
For Gogs
Effectively removes roundworms
Tasty, easy to feed
Convenient dosage cup enclosed
Veterinarian Approved
NET 4 FL. OZ. (118mL)